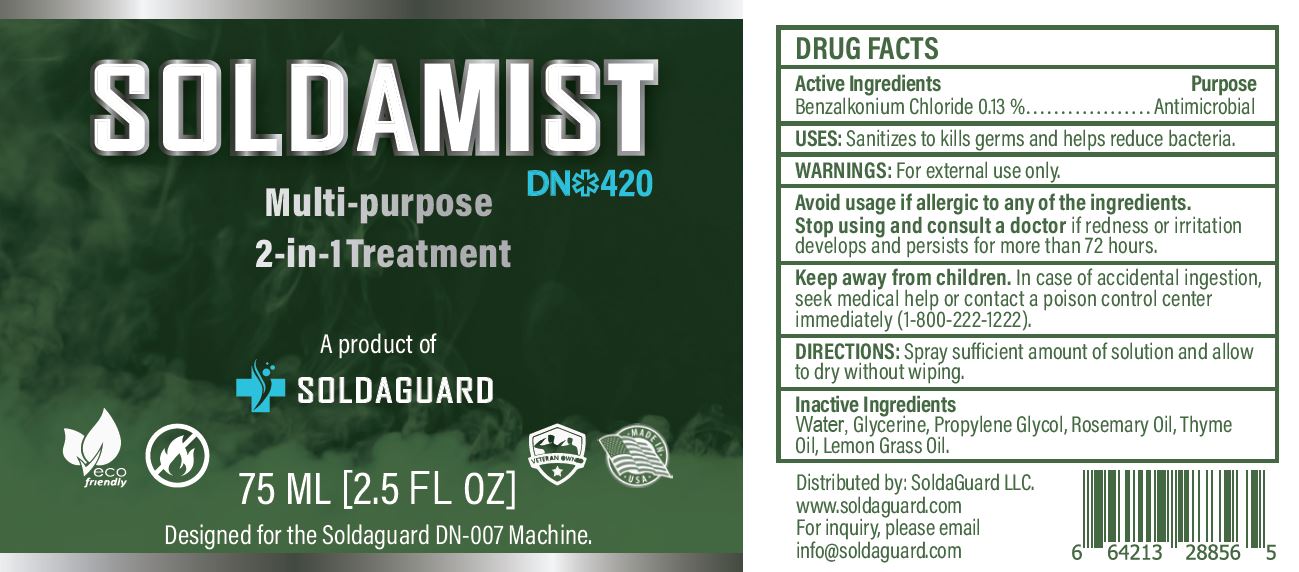 DRUG LABEL: SOLDAMIST

NDC: 77015-420 | Form: SPRAY
Manufacturer: 3VETS LLC
Category: otc | Type: HUMAN OTC DRUG LABEL
Date: 20230110

ACTIVE INGREDIENTS: BENZALKONIUM CHLORIDE 0.13 g/100 mL
INACTIVE INGREDIENTS: WATER; GLYCERIN; PROPYLENE GLYCOL; ROSEMARY OIL; THYME OIL; WEST INDIAN LEMONGRASS OIL

3VETS LLC - SOLDAMIST DN-420, MULTI-PURPOSE 2-IN-1 TREATMENT (77015-420)

ACTIVE INGREDIENT

BENZALKONIUM CHLORIDE 0.13%

PURPOSE

ANTIMICROBIAL

USES

Sanitizes to kills germs and helps reduce bacteria.

WARNINGS

For external use only.

Avoid usage if allergic to any of the ingredients.

Stop using and consult a doctor if redness or irritation develops and persists for more than 72 hours.

KEEP OUT OF REACH OF CHILDREN

Keep away from children. In case of accidental ingestion, seek medical help or contact a poison control center immediately (1-800-222-1222).

DIRECTIONS

Spray sufficient amount of solution and allow to dry without wiping.

INACTIVE INGREDIENTS

Water, Glycerine, Propylene Glycol, Rosemary Oil, Thyme Oil, Lemon Grass Oil.